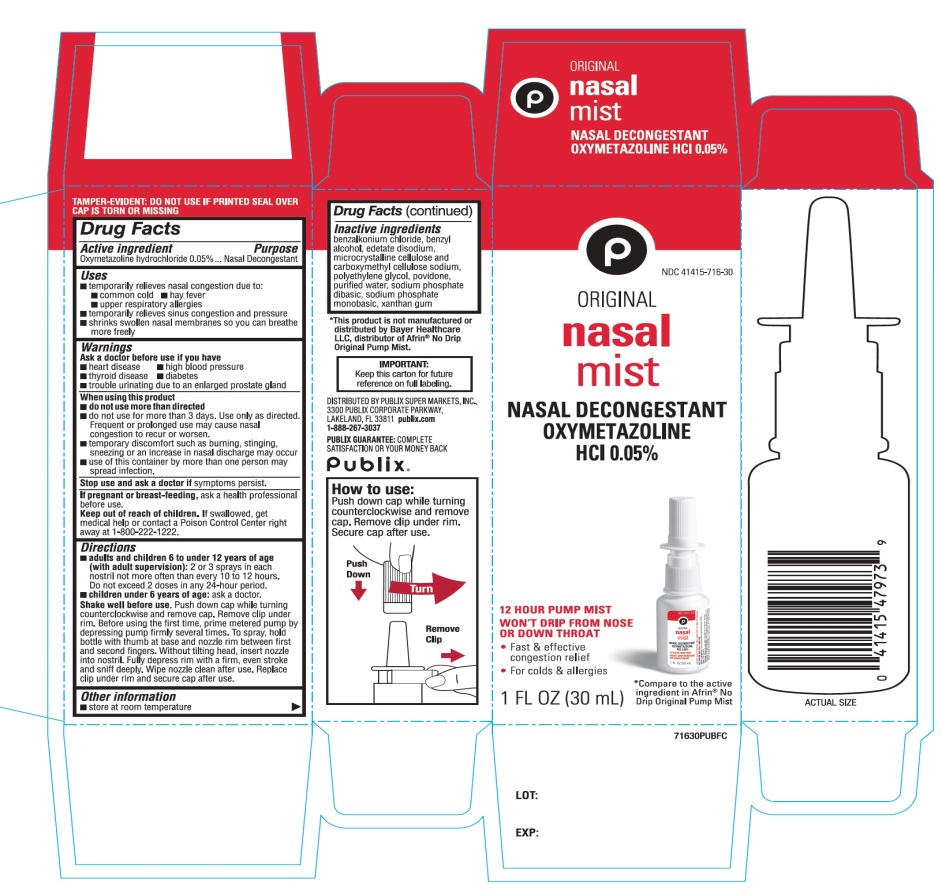 DRUG LABEL: Publix
NDC: 41415-716 | Form: SPRAY
Manufacturer: PUBLIX SUPER MARKETS, INC
Category: otc | Type: HUMAN OTC DRUG LABEL
Date: 20251028

ACTIVE INGREDIENTS: OXYMETAZOLINE HYDROCHLORIDE 0.05 g/100 mL
INACTIVE INGREDIENTS: BENZALKONIUM CHLORIDE; BENZYL ALCOHOL; EDETATE DISODIUM; MICROCRYSTALLINE CELLULOSE; CARBOXYMETHYLCELLULOSE SODIUM, UNSPECIFIED; POLYETHYLENE GLYCOL, UNSPECIFIED; POVIDONE, UNSPECIFIED; WATER; SODIUM PHOSPHATE, DIBASIC, UNSPECIFIED FORM; SODIUM PHOSPHATE, MONOBASIC, UNSPECIFIED FORM; XANTHAN GUM

Publix Nasal Mist Oxymetazoline HCl Drug Facts

Active ingredient

Oxymetazoline hydrochloride 0.05%

Purpose

Nasal Decongestant

Uses

for the temporarily relief of nasal congestion due to:

- common cold
- hay fever
- upper respiratory allergies
- temporarily relieves sinus congestion and pressure
- shrinks swollen nasal membranes so you can breathe more freely

Ask a doctor before use if you have

- heart disease
- high blood pressure
- diabetes
- thyroid disease
- trouble urinating due to an enlarged prostate gland

When using this product

- do not use more than directed
- do not use for more than 3 days. Use only as directed. Frequent or prolonged use may cause nasal congestion to recur or worsen.
- temporary discomfort such as burning, stinging, sneezing or an increase in nasal discharge may occur
- use of this container by more than one person may spread infection

Stop use and ask a doctor if

symptoms persist

If pregnant or breast-feeding,

ask a health professional before use.

Keep out of reach of children.

If swallowed, get medical help or contact a Poison Control Center right away at (1-800-222-1222).

Directions

- adults and children 6 to under 12 years of age (with adult supervision):2 or 3 sprays in each nostril not more often than every 10 to 12 hours. Do not exceed 2 doses in any 24-hour period.
- children under 6 years of age:ask a doctor

Sake well before use:Before using the first time, remove the protective cap from the tip by pressing and twisting off the cap. Rotate the lock tab to align arrow marks to unlock the pump. Prime metered pump by depressing pump firmly several times. To spray, hold bottle with thumb at base and nozzle between first and second fingers. Without tilting head, insert nozzle into nostril. Fully depress rim with a firm, even stroke and sniff deeply. Wipe nozzle clean after use. Lock the pump by ensuring that arrow marks are not aligned and replace the protective cap on tip

Other information

- store at room temperature

How to use:

Push down cap while turning counterclockwise and remove cap. Remove clip under rim. Secure cap after use.

Inactive ingredients

benzalkonium chloride, benzyl alcohol, edetate disodium, microcrystalline cellulose and carboxymethyl cellulose sodium, polyethylene glycol, povidone, purified water, sodium phosphate dibasic, sodium phosphate monobasic, xanthan gum.

Questions or comments?

1-888-267-3037

Principal Display Panel

Publix®

NDC# 41415-716-30

Compare to the active ingredient in Afrin® No Drip Original Pump Mist

ORIGINAL

nasal mist

NASAL DECONGESTANT

OXYMETAZOLINE HCL 0.05%

12 HOUR PUMP MIST WON’T DRIP FROM NOSE OR DOWN THROAT

- Fast & effective congestion relief
- For colds & allergies

1 FL OZ (30 mL)

IMPORTANT:Keep this carton for future reference on full labeling.

DISTRIBUTED BY PUBLIX SUPER MARKETS, INC.,

3300 PUBLIX CORPORATE PARKWAY,

LAKELAND, FL 33811

1-888-267-3037 publix.com

PUBLIX GUARANTEE:COMPLETE SATISFACTION OR YOUR MONEY BACK

*This product is not manufactured or distributed by Bayer Healthcare LLC, distributer of Afrin®Original.